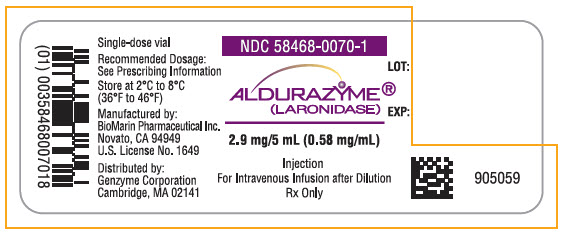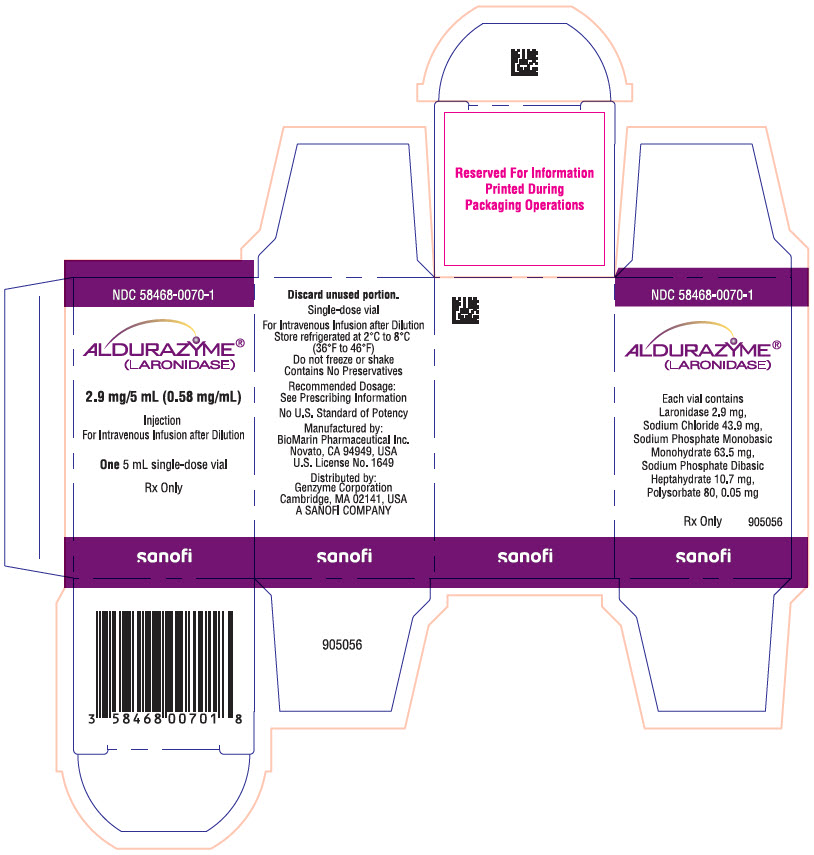 DRUG LABEL: ALDURAZYME
NDC: 58468-0070 | Form: INJECTION, SOLUTION, CONCENTRATE
Manufacturer: Genzyme Corporation
Category: prescription | Type: HUMAN PRESCRIPTION DRUG LABEL
Date: 20231222

ACTIVE INGREDIENTS: LARONIDASE 2.9 mg/5 mL

HIGHLIGHTS OF PRESCRIBING INFORMATION

These highlights do not include all the information needed to use ALDURAZYME safely and effectively. See full prescribing information for ALDURAZYME.
ALDURAZYME (laronidase) injection, for intravenous use
Initial U.S. Approval: 2003

WARNING: HYPERSENSITIVITY REACTIONS INCLUDING ANAPHYLAXIS, and ACUTE RESPIRATORY COMPLICATIONS ASSOCIATED WITH ADMINISTRATION

See full prescribing information for complete boxed warning.

- Appropriate medical monitoring and support measures, including cardiopulmonary resuscitation equipment, should be readily available. If a severe hypersensitivity reaction occurs, discontinue ALDURAZYME immediately and initiate appropriate medical treatment. (5.1)
- Patients with compromised respiratory function or acute respiratory disease may be at risk of serious acute exacerbation of their respiratory compromise due to infusion reactions and require additional monitoring. Appropriate respiratory support should be available during infusion. (5.2)

RECENT MAJOR CHANGES

Boxed Warning | 12/2023
Dosage and Administration (2.2, 2.3, 2.5, 2.6) | 12/2023
Warnings and Precautions (5.1, 5.4) | 12/2023

1 INDICATIONS AND USAGE

ALDURAZYME is a hydrolytic lysosomal glycosaminoglycan (GAG)-specific enzyme indicated for the treatment of adult and pediatric patients with Hurler and Hurler-Scheie forms of Mucopolysaccharidosis I (MPS I) and for the treatment of patients with the Scheie form of MPS I who have moderate to severe symptoms. (1)

Limitations of Use:

- The risks and benefits of treating mildly affected patients with the Scheie form have not been established. (1)
- ALDURAZYME has not been evaluated for effects on the central nervous system manifestations of the disorder. (1)

2 DOSAGE AND ADMINISTRATION

- For pretreatment recommendations, see Full Prescribing Information. (2.1)
- The recommended dosage is 0.58 mg/kg administered once weekly as an intravenous infusion. (2.2)
- For dosage and administration modifications due to hypersensitivity reactions or infusion-associated reactions (IARs), see Full Prescribing Information. (2.3)
- For instructions on preparation, storage, and administration, see Full Prescribing Information. (2.4, 2.5, 2.6)

3 DOSAGE FORMS AND STRENGTHS

Injection: 2.9 mg/5 mL (0.58 mg/mL) of laronidase in a single-dose vial. (3)

4 CONTRAINDICATIONS

None. (4)

5 WARNINGS AND PRECAUTIONS

- Risk of Acute Respiratory Complications: Patients with acute febrile or respiratory illness at the time of ALDURAZYME infusion may be at greater risk for infusion reactions. Consider delaying ALDURAZYME infusion. Sleep apnea is common in MPS I patients. Consider evaluating airway patency prior to initiation of treatment with ALDURAZYME. Appropriate respiratory support should be available during infusion. (5.2)
- Risk of Acute Cardiorespiratory Failure: Patients susceptible to fluid overload may be at increased risk for serious exacerbation of their cardiac or respiratory status during infusions. Consider a decreased total infusion volume and infusion rate when administering ALDURAZYME to these patients. Appropriate medical monitoring and support measures should be available during infusion. (2.2, 5.3)
- Infusion Reactions: If severe IARs occur, discontinue ALDURAZYME and initiate appropriate medical treatment. (5.4)

6 ADVERSE REACTIONS

Most common adverse reactions (≥10%) in patients:

- 6 months of age and older are: infusion reactions (pyrexia, chills, blood pressure increased, tachycardia, and oxygen saturation decreased). (6.1)
- 6 years and older are: rash, upper respiratory tract infection, injection site reaction, hyperreflexia, paresthesia, flushing, and poor venous access. (6.1)

To report SUSPECTED ADVERSE REACTIONS, contact Genzyme at 1-800-745-4447 or FDA at 1-800-FDA-1088 or www.fda.gov/medwatch.

FULL PRESCRIBING INFORMATION

WARNING: HYPERSENSITIVITY REACTIONS INCLUDING ANAPHYLAXIS, and ACUTE RESPIRATORY COMPLICATIONS ASSOCIATED WITH ADMINISTRATION

Hypersensitivity Reactions Including Anaphylaxis

Patients treated with ALDURAZYME have experienced life-threatening hypersensitivity reactions, including anaphylaxis. Appropriate medical monitoring and support measures, including cardiopulmonary resuscitation equipment, should be readily available during ALDURAZYME administration. If a severe hypersensitivity reaction (e.g., anaphylaxis) occurs, discontinue ALDURAZYME immediately and initiate appropriate medical treatment. In patients with severe hypersensitivity reactions, a desensitization procedure to ALDURAZYME may be considered [see Warnings and Precautions (5.1)].

Acute Respiratory Complications Associated with Administration

Patients with compromised respiratory function or acute respiratory disease may be at risk of serious acute exacerbation of their respiratory compromise due to infusion reactions and require additional monitoring [see Warnings and Precautions (5.2)].

1 INDICATIONS AND USAGE

ALDURAZYME® is indicated for the treatment of:

- adult and pediatric patients with Hurler and Hurler-Scheie forms of Mucopolysaccharidosis I (MPS I) and
- patients with the Scheie form of MPS I who have moderate to severe symptoms.

Limitations of Use

- The safety and effectiveness of treating mildly affected patients with the Scheie form have not been established.
- The effect of ALDURAZYME on central nervous system manifestations of the disorder has not been determined.

2 DOSAGE AND ADMINISTRATION

2.1 Recommendations Prior to ALDURAZYME Treatment

Premedication

Prior to ALDURAZYME administration, consider premedicating with antihistamines, with or without antipyretics, 60 minutes before the start of infusion [see Warnings and Precautions (5.1, 5.4)].

Medical Support

Appropriate medical monitoring and support measures, including cardiopulmonary resuscitation equipment, should be readily available during ALDURAZYME administration.

2.2 Recommended Dosage and Administration

The recommended dosage of ALDURAZYME is 0.58 mg/kg (actual body weight) administered once weekly as an intravenous infusion.

ALDURAZYME injection must be diluted with 0.9% Sodium Chloride Injection to a final volume of 50 mL, 100 mL or 250 mL as determined by the patient's body weight and cardiopulmonary condition:

Patients with a body weight equal to or greater than 2 kg and less than 4 kg should receive a total volume of 50 mL; patients with a body weight equal to or greater than 4 kg and up to 20 kg should receive a total volume of 100 mL; and those patients with a body weight greater than 20 kg should receive a total volume of 250 mL [see Dosage and Administration (2.6)]. For patients with underlying cardiac or respiratory compromise and weighing up to 30 kg, physicians may consider diluting ALDURAZYME in a volume of 100 mL and administering at a decreased infusion rate [see Dosage and Administration (2.6)].

The initial infusion rate of ALDURAZYME is 10 mcg/kg/hr and may be increased every 15 minutes during the first hour, as tolerated, to a maximum infusion rate of 200 mcg/kg/hr. The maximum rate is then maintained for the remainder of the infusion (2 to 3 hours) [see Dosage and Administration (2.6), Warnings and Precautions (5.2, 5.3)].

If one or more doses are missed, restart ALDURAZYME treatment as soon as possible and maintain the 1-week interval between infusions thereafter. Do not double a dose to compensate for a missed dose.

2.3 Administration Modifications due to Hypersensitivity or Infusion Associated Reaction

In the event of a severe hypersensitivity reaction (e.g. anaphylaxis) or severe infusion-associated reaction (IAR), immediately discontinue ALDURAZYME administration and initiate appropriate medical treatment. For additional recommendations in the event of a severe hypersensitivity reaction, [see Warnings and Precautions (5.1)].

In the event of a mild to moderate hypersensitivity reaction or a mild to moderate IAR, consider temporarily holding the infusion for 15 to 30 minutes, or slowing the infusion rate by 25% to 50% [see Dosage and Administration (2.6)], and initiating appropriate medical treatment [see Warnings and Precautions (5.1, 5.4)].

- If symptoms persist despite holding or slowing the infusion, stop the infusion and monitor the patient. Consider re-initiating the infusion within 7 to 14 days using the incremental rate steps table [see Dosage and Administration (2.6)], up to 25% or 50% of the rate at which the reaction occurred with appropriate premedication.
- If symptoms subside after holding the infusion, resume infusion at a 25% to 50% reduced rate as tolerated. Alternatively, if symptoms subside after slowing the infusion, complete infusion at the reduced rate as tolerated.
- Starting with next infusion, increase the infusion rate by increments of 25% as tolerated until the recommended infusion rate is reached. Closely monitor the patient.

2.4 Preparation Instructions

Prepare ALDURAZYME using low-protein-binding containers. There is no information on the compatibility of diluted ALDURAZYME with glass containers. Dilute ALDURAZYME in the following manner using aseptic technique:

1. Determine the infusion bag volume and number of ALDURAZYME vials to be diluted based on actual body weight in kg and the recommended dose [see Dosage and Administration (2.2)]. Round the number of vials up to the next whole number.
2. Remove the appropriate number of ALDURAZYME vials from the refrigerator and allow the vials to reach room temperature 20°C to 25°C (68°F to 77°F) before use. Do not heat or microwave the vials.
3. Visually inspect the solution in each vial for particulate matter and discoloration. The ALDURAZYME solution should be clear to slightly opalescent and colorless to pale yellow. Some translucency may be present in the solution. Discard if the solution is discolored or if visible particulate matter is present.
4. Withdraw and discard a volume of the 0.9% Sodium Chloride Injection from an infusion bag, equal to the volume of ALDURAZYME to be added.
5. Slowly withdraw the calculated volume of ALDURAZYME from the appropriate number of vials using caution to avoid excessive agitation. Do not use a filter needle, as this may cause agitation. Agitation may denature ALDURAZYME, rendering it biologically inactive. Discard any unused solution remaining in the vial.
6. Slowly add the ALDURAZYME solution to the 0.9% Sodium Chloride Injection solution through the port of the infusion bag and avoid agitation. Do not use a filter needle.
7. Gently rotate the infusion bag to ensure proper distribution of ALDURAZYME. Do not shake the infusion bag.

2.5. Storage Instruction for the Diluted Solution

If the diluted ALDURAZYME solution is not used immediately:

- Refrigerate the diluted solution at 2°C to 8°C (36°F to 46°F) for up to 36 hours. Discard any unused ALDURAZYME diluted solution after 36 hours. Do not store the diluted solution at room temperature.
- The solution must be infused within 8 hours after removal from the refrigerator, inclusive of the total infusion time, or discarded.

2.6 Administration Instructions

1. Use an infusion set equipped with a low-protein-binding, 0.2 micron, in-line filter to administer the diluted ALDURAZYME solution.
2. The total volume of infusion [see Dosage and Administration (2.2)] should be administered over approximately 3 to 4 hours as tolerated per the infusion rate steps outlined in Table 1 below.
3. At the end of the infusion, flush the infusion line with 0.9% Sodium Chloride Injection, using the same infusion rate as the one used for the last part of the infusion.
4. Do not infuse ALDURAZYME in the same intravenous line with other products.

Table 1: Incremental Infusion Rate Steps and Volumes for ALDURAZYME® Infusion by Patient Weight
Patient Weight Range | Total Infusion Volume | Step 1 10 mcg/kg/hr | Step 2 20 mcg/kg/hr | Step 3 50 mcg/kg/hr | Step 4 100 mcg/kg/hr | Step 5 200 mcg/kg/hr
Patient Weight Range | Total Infusion Volume | Infusion Rate in mL/hour
≥2 to <4 kg | 50 mL | 1 | 2 | 4 | 8 | 16
≥4 to <20 kg | 100 mL | 2 | 4 | 8 | 16 | 32
≥20 kg | 250 mL | 5 | 10 | 20 | 40 | 80

Start infusion at rate in Step 1. In the absence of infusion-associated reactions after vital sign assessment, increase infusion rate sequentially per the steps in Table 1 every 15 minutes to reach the target rate in Step 5. Continue Step 5 until infusion is completed. The total infusion time is approximately 3 to 4 hours.

3 DOSAGE FORMS AND STRENGTHS

Injection: 2.9 mg/5 mL (0.58 mg/mL) of laronidase as a colorless to pale yellow, clear to slightly opalescent solution in a single-dose vial.

4 CONTRAINDICATIONS

None.

5 WARNINGS AND PRECAUTIONS

5.1 Hypersensitivity Reactions Including Anaphylaxis

Hypersensitivity reactions including anaphylaxis have been reported in patients during or up to 3 hours after ALDURAZYME infusions. Some of these reactions were life-threatening and included respiratory failure, respiratory distress, stridor, tachypnea, bronchospasm, obstructive airways disorder, hypoxia, hypotension, bradycardia, and urticaria.

In clinical studies and postmarketing safety experience with ALDURAZYME, approximately 1% of patients experienced severe or serious hypersensitivity reactions. In patients with MPS I, pre-existing upper airway obstruction may have contributed to the severity of some reactions.

Prior to ALDURAZYME administration, consider premedicating patients with antihistamines, with or without antipyretics, 60 minutes before the start of infusion. Appropriate medical monitoring and support measures, including cardiopulmonary resuscitation equipment, should be readily available during ALDURAZYME administration. Because of the potential for recurrent reactions, some patients who experience initial severe reactions may require prolonged observation.

- If a severe hypersensitivity reaction (e.g., anaphylaxis) occurs, discontinue ALDURAZYME immediately and initiate appropriate medical treatment. Exercise caution if epinephrine is being considered for use in patients with MPS I due to the increased prevalence of coronary artery disease in these patients. Interventions have included resuscitation, mechanical ventilatory support, emergency tracheotomy, hospitalization, and treatment with inhaled beta-adrenergic agonists, epinephrine, and intravenous corticosteroids [see Adverse Reactions (6)].
- Consider the risks and benefits of re-administering ALDURAZYME following severe hypersensitivity reactions (including anaphylaxis). Patients may be rechallenged using slower infusion rates. In patients with severe hypersensitivity reaction, desensitization measures to ALDURAZYME may be considered. If the decision is made to readminister ALDURAZYME, ensure the patient tolerates the infusion. If the patient tolerates the infusion, the rate may be increased to reach the recommended rate.
- If a mild or moderate hypersensitivity reaction occurs, consider temporarily holding the infusion or slowing the infusion rate [see Dosage and Administration (2.3)].

5.2 Acute Respiratory Complications Associated with Administration

One patient with acute bronchitis and hypoxia experienced increased tachypnea during the first ALDURAZYME infusion that resolved without intervention. The patient's respiratory symptoms returned within 30 minutes of completing the infusion and responded to bronchodilator therapy. Approximately 6 hours after the infusion, the patient experienced coughing, then respiratory arrest, and died.

Patients with an acute febrile or respiratory illness at the time of ALDURAZYME infusion may be at greater risk for infusion reactions. Careful consideration should be given to the patient's clinical status prior to administration of ALDURAZYME and consider delaying ALDURAZYME infusion.

Sleep apnea is common in MPS I patients. Consider evaluating airway patency prior to initiation of treatment with ALDURAZYME. Patients using supplemental oxygen or continuous positive airway pressure (CPAP) during sleep should have these treatments readily available during infusion in the event of an infusion reaction, or extreme drowsiness/sleep induced by antihistamine use.

5.3 Acute Cardiorespiratory Failure

In postmarketing experience, reports of acute cardiorespiratory failure have been reported with ALDURAZYME treatment [see Adverse Reactions (6.2)]. Patients susceptible to fluid overload, or patients with acute underlying respiratory illness or compromised cardiac and/or respiratory function for whom fluid restriction is indicated may be at increased risk of serious exacerbation of their cardiac or respiratory status during infusions. Consider a decreased total infusion volume and infusion rate when administering ALDURAZYME to these patients [see Dosage and Administration (2.2)]. Appropriate medical monitoring and support measures should be readily available during ALDURAZYME infusion, and some patients may require prolonged observation times that should be based on the individual needs of the patient.

5.4 Infusion-Associated Reactions

ALDURAZYME may cause infusion-associated reactions (IARs). Prior to ALDURAZYME administration, consider pre-medicating with antihistamines, with or without antipyretics, 60 minutes before the start of infusion to reduce the risk of IARs. However, IARs may still occur in patients after receiving pre-medication.

- If a severe IAR occurs, discontinue ALDURAZYME immediately and initiate appropriate medical treatment. Consider the risks and benefits of re-administering ALDURAZYME following a severe IAR. Patients may be re-challenged using slower infusion rates. Once a patient tolerates the infusion, the infusion rate may be increased to reach the recommended infusion rate.
- If a mild or moderate IAR occurs, consider temporarily holding the infusion or slowing the infusion rate [see Dosage and Administration (2.3), and Adverse Reactions (6.1, 6.2)].

6 ADVERSE REACTIONS

Serious and or clinically significant adverse reactions described elsewhere in labeling include:

- Hypersensitivity Reactions Including Anaphylaxis [see Warnings and Precautions (5.1)]
- Acute Respiratory Complications Associated with Administration [see Warnings and Precautions (5.2)]
- Acute Cardiorespiratory Failure [see Warnings and Precautions (5.3)]
- Infusion-Associated Reactions [see Warnings and Precautions (5.4)]

6.1 Clinical Trials Experience

Because clinical trials are conducted under widely varying conditions, adverse reaction rates observed in the clinical trials of a drug cannot be directly compared to rates in the clinical trials of another drug and may not reflect the rates observed in clinical practice.

Serious adverse reactions reported with ALDURAZYME treatment during clinical trials were anaphylactic and hypersensitivity reactions. The most common adverse reactions were infusion reactions. The frequency of infusion reactions decreased over time with continued use of ALDURAZYME, and the majority of reactions were classified as being mild to moderate in severity.

Clinical Trials in Patients 6 Years and Older

A 26-week, double-blind, placebo-controlled clinical study (Study 1) of ALDURAZYME was conducted in 45 patients with MPS I, ages 6 to 43 years old, gender evenly distributed (N=23 females and 22 males). Of these 45 patients, 1 was clinically assessed as having Hurler form, 37 Hurler-Scheie, and 7 Scheie. Patients were randomized to receive either 0.58 mg/kg intravenously of ALDURAZYME per week for 26 weeks or placebo. All patients were treated with antipyretics and antihistamines prior to the infusions. Infusion reactions were reported in 32% (7 of 22) of ALDURAZYME-treated patients.

The most common adverse reactions reported in patients who received ALDURAZYME were flushing, pyrexia, headache, and rash. Flushing occurred in 5 patients (23%) receiving ALDURAZYME; the other reactions were less frequent. Less common infusion reactions included angioedema (including face edema), hypotension, paresthesia, feeling hot, hyperhidrosis, tachycardia, vomiting, back pain, and cough. Other reported adverse reactions included bronchospasm, dyspnea, urticaria and pruritus.

Table 2 enumerates adverse reactions and selected laboratory abnormalities that occurred during the 26-week placebo-controlled study (Study 1) that were reported in at least 2 patients more in the ALDURAZYME group than in the placebo group.

Table 2: Adverse Reactions that Occurred in at Least 2 Patients More in the ALDURAZYME Group than in the Placebo Group Among Adult and Pediatric Patients with MPS I in Study 1
 | ALDURAZYME N=22 n (%) | Placebo N=23 n (%)
Blood and lymphatic system disorders
Thrombocytopenia | 2 (9) | 0
Eye disorders
Corneal opacity | 2 (9) | 0
General disorders and administration site conditions
Chest pain | 2 (9) | 0
Face edema | 2 (9) | 0
Gravitational edema | 2 (9) | 0
Injection site pain | 2 (9) | 0
Injection site reaction | 4 (18) | 2 (9)
Hepatobiliary disorders
Hyperbilirubinemia | 2 (9) | 0
Infections and infestations
Abscess | 2 (9) | 0
Upper respiratory tract infection | 7 (32) | 4 (17)
Nervous system disorders
Hyperreflexia | 3 (14) | 0
Paresthesia | 3 (14) | 1 (4)
Skin and subcutaneous tissue disorders
Rash | 8 (36) | 5 (22)
Vascular disorders
Hypotension | 2 (9) | 0
Poor venous access | 3 (14) | 0

All 45 patients who completed the placebo-controlled study (Study 1) continued treatment in an open-label, uncontrolled extension study (Study 2). All patients received ALDURAZYME 0.58 mg/kg of body weight once weekly for up to 182 weeks. The most serious adverse reactions reported with ALDURAZYME infusions in Study 2 were anaphylactic and hypersensitivity reactions [see Warnings and Precautions (5)]. One patient had an anaphylactic reaction consisting of urticaria and airway obstruction and tested positive for both ALDURAZYME-specific IgG and IgE binding antibodies and complement activation. The most common adverse reactions requiring intervention were infusion reactions reported in 49% (22 of 45) of patients treated with ALDURAZYME. The most common adverse reactions reported in patients who received ALDURAZYME were rash (13%), flushing (11%), pyrexia (11%), headache (9%), abdominal pain or discomfort (9%), and injection site reaction (9%). Less commonly reported infusion reactions included nausea (7%), diarrhea (7%), feeling hot or cold (7%), vomiting (4%), pruritus (4%), arthralgia (4%), and urticaria (4%). Additional common adverse reactions included back pain and musculoskeletal pain.

Clinical Trials in Patients 6 Years and Younger

Study 3 was a 52-week, open-label, uncontrolled study of 20 MPS I patients, ages 6 months to 5 years old (at enrollment). Sixteen patients were clinically assessed as having the Hurler form, and 4 had the Hurler-Scheie form. All 20 patients received ALDURAZYME at 0.58 mg/kg of body weight once weekly for 26 weeks and up to 52 weeks. All patients were treated with antipyretics and antihistamines prior to the infusions.

The nature and severity of infusion reactions were similar between the older and less severely affected patients (Studies 1 and 2) and the younger, more severely affected patients (Study 3). The most commonly reported adverse reactions in Study 3 were infusion reactions reported in 35% (7 of 20) of patients and included pyrexia (30%), chills (20%), blood pressure increased (10%), tachycardia (10%), and oxygen saturation decreased (10%). Other commonly reported infusion reactions occurring in ≥5% of patients were pallor, tremor, respiratory distress, wheezing, crepitations (pulmonary), pruritus, and rash.

6.2 Postmarketing Experience

The following adverse reactions have been identified during post approval use of ALDURAZYME. Because these reactions are reported voluntarily from a population of uncertain size, it is not always possible to reliably estimate their frequency or establish a causal relationship to drug exposure.

In postmarketing experience with ALDURAZYME, severe and serious infusion reactions have been reported, some of which were life-threatening, including anaphylactic shock [see Warnings and Precautions (5.1)] and laryngeal edema.

Adverse reactions resulting in death reported in the postmarketing setting with ALDURAZYME treatment included cardiorespiratory arrest, respiratory failure, cardiac failure, and pneumonia. These events have been reported in MPS I patients with underlying disease [see Warnings and Precautions (5.3)].

Additional adverse reactions included fatigue, peripheral edema, erythema and cyanosis.

There have been a small number of reports of extravasation in patients treated with ALDURAZYME. There have been no reports of tissue necrosis associated with extravasation.

Immunogenicity: Anti-Drug Antibody-Associated Adverse Reactions Including Anaphylaxis

In the MPS I Registry and other postmarketing setting, laronidase-specific IgE and/or IgG antibodies appeared to be associated with anaphylaxis and suspected hypersensitivity reactions in ALDURAZYME-treated patients [see Clinical Pharmacology (12.6)].

8 USE IN SPECIFIC POPULATIONS

8.1 Pregnancy

Pregnancy Exposure Registry

An MPS I Registry has been established. Pregnant women with MPS I and healthcare providers are encouraged to contact the pregnancy sub-registry by visiting www.registrynxt.com or calling 1-800-745-4447 ext. 15500.

Risk Summary

Available data from the MPS I Registry pregnancy sub-registry, published case reports, and the global pharmacovigilance database with ALDURAZYME use in more than 30 pregnant women have not identified a drug-associated risk of major birth defects, miscarriage, or adverse maternal or fetal outcomes. The continuation of treatment for MPS I during pregnancy should be individualized to the pregnant woman. Untreated MPS I may result in adverse pregnancy and infant outcomes (see Clinical Considerations). No evidence of fetal harm has been observed in rats when laronidase was administered during organogenesis at doses up to 6.2 times the recommended human dose (see Data).

The background risk of major birth defects and miscarriage for the indicated population is unknown. All pregnancies have a background risk of birth defect, loss, or other adverse outcomes. In the U.S. general population, the estimated background risk of major birth defects and miscarriage in clinically recognized pregnancies is 2% to 4% and 15% to 20%, respectively.

Clinical Considerations

Disease-Associated Maternal and/or Embryo-Fetal Risk

Pregnancy can exacerbate preexisting clinical manifestations of MPS and lead to adverse pregnancy outcomes for both mother and fetus.

Data

Animal Data

When laronidase was administered to pregnant female rats during organogenesis (gestation days [GD] 7-17) at doses of 0, 0.036, 0.36 or 3.6 mg/kg/day intravenously (equivalent to 7.3, 73.1, 730.8 units/kg/day) decreased maternal body weight gains and food consumption were observed with no corresponding effects on reproductive and litter parameters including number and distribution of corpora lutea, implantations and early and late resorptions at doses up to 3.6 mg/kg/day (6.2 times the recommended human dose of 0.58 mg/kg on a mg/kg basis). Laronidase has not been evaluated for effects on embryo-fetal development in any other species.

8.2 Lactation

Risk Summary

Available information from one mother:infant pair are insufficient to evaluate the presence or absence of laronidase in human milk. No adverse effects have been reported in breastfed infants in postmarketing cases of ALDURAZYME use in lactating women. The developmental and health benefits of breastfeeding should be considered along with the mother's clinical need for ALDURAZYME and any potential adverse effects on the breastfed child from ALDURAZYME or from the underlying maternal condition.

Lactating women with MPS I and healthcare providers are encouraged to contact the MPS I Registry by visiting www.registrynxt.com or calling 1-800-745-4447 ext. 15500.

8.4 Pediatric Use

The safety and effectiveness of ALDURAZYME have been established for the treatment of pediatric patients with Hurler and Hurler-Scheie forms of Mucopolysaccharidosis I (MPS I) and the treatment of pediatric patients with the Scheie form of MPS I who have moderate to severe symptoms. The safety and effectiveness ALDURAZYME for the treatment of mildly affected pediatric patients with the Scheie form have not been established.

Use of ALDURAZYME for these indications is supported by evidence from an adequate and well-controlled clinical study (Study1) with an open label extension (Study 2) in adult and pediatric patients with MPS I, and from an open label, uncontrolled clinical study in pediatric patients with MPS I, 6 months to 5 years of age (Study 3). The safety and effectiveness of ALDURAZYME in pediatric patients 6 months of age to 5 years of age was found to be similar to pediatric patients 6 to 18 years of age and adults for these indications [see Adverse Reactions (6.1), Clinical Studies (14)].

8.5 Geriatric Use

Clinical studies of ALDURAZYME did not include patients 65 years of age and older to determine if they respond differently from younger patients.

11 DESCRIPTION

ALDURAZYME (laronidase) is a polymorphic variant of the human enzyme α-L-iduronidase that is produced by recombinant DNA technology in a Chinese hamster ovary cell line. α-L-iduronidase (glycosaminoglycan α-L-iduronohydrolase, EC 3.2.1.76) is a lysosomal hydrolase that catalyzes the hydrolysis of terminal α-L-iduronic acid residues of dermatan sulfate and heparan sulfate.

Laronidase is a glycoprotein with a molecular weight of approximately 83 kD. The predicted amino acid sequence of the recombinant form, as well as the nucleotide sequence that encodes it, are identical to a polymorphic form of human α-L-iduronidase. The recombinant protein is comprised of 628 amino acids after cleavage of the N-terminus and contains 6 N-linked oligosaccharide modification sites. Two oligosaccharide chains terminate in mannose-6-phosphate sugars. ALDURAZYME has a specific activity of approximately 172 U/mg.

ALDURAZYME, for intravenous infusion, is supplied as a sterile, nonpyrogenic, colorless to pale yellow, clear to slightly opalescent solution that must be diluted prior to administration in 0.9% Sodium Chloride Injection, USP. The solution in each vial contains a nominal laronidase concentration of 0.58 mg/mL and a pH of approximately 5.5. The extractable volume of 5 mL from each vial provides 2.9 mg laronidase, 43.9 mg sodium chloride, 63.5 mg sodium phosphate monobasic monohydrate, 10.7 mg sodium phosphate dibasic heptahydrate, and 0.05 mg polysorbate 80. ALDURAZYME does not contain preservatives; vials are for single dose only.

12 CLINICAL PHARMACOLOGY

12.1 Mechanism of Action

Mucopolysaccharide storage disorders are caused by the deficiency of specific lysosomal enzymes required for the catabolism of glycosaminoglycans (GAG). Mucopolysaccharidosis I (MPS I) is characterized by the deficiency of α-L-iduronidase, a lysosomal hydrolase which catalyzes the hydrolysis of terminal α-L-iduronic acid residues of dermatan sulfate and heparan sulfate. Reduced or absent α-L-iduronidase activity results in the accumulation of the GAG substrates, dermatan sulfate and heparan sulfate, throughout the body and leads to widespread cellular, tissue, and organ dysfunction.

The rationale of ALDURAZYME therapy in MPS I is to provide exogenous enzyme for uptake into lysosomes and increase the catabolism of GAG. ALDURAZYME uptake by cells into lysosomes is most likely mediated by the mannose-6-phosphate-terminated oligosaccharide chains of laronidase binding to specific mannose-6-phosphate receptors.

Because many proteins in the blood are restricted from entry into the central nervous system (CNS) by the blood brain barrier, effects of intravenously administered ALDURAZYME on cells within the CNS cannot be inferred from activity in sites outside the CNS. The ability of ALDURAZYME to cross the blood brain barrier has not been evaluated in animal models or in clinical studies.

12.2 Pharmacodynamics

The pharmacodynamic effect of ALDURAZYME was assessed by reductions in urinary GAG levels. The responsiveness of urinary GAG to dosage alterations of ALDURAZYME is unknown, and the relationship of urinary GAG to other measures of clinical response has also not been established [see Clinical Studies (14)].

12.3 Pharmacokinetics

The pharmacokinetics of laronidase were evaluated in 6-year-old or older patients (N=10 to 12) with MPS I who received 0.58 mg/kg of body weight once weekly of ALDURAZYME as a 4-hour infusion in the placebo-controlled clinical study (Study 1). After the 1st, 12th, and 26th weekly infusions, the mean maximum plasma concentrations (Cmax) ranged from 1.2 to 1.7 mcg/mL for the 3 time points. The mean area under the plasma concentration-time curve (AUC∞) ranged from 4.5 to 6.9 mcg ∙ hour/mL. The mean volume of distribution (Vz) ranged from 0.24 to 0.60 L/kg. Mean plasma clearance (CL) ranged from 1.7 to 2.7 mL/min/kg, and the mean elimination half-life (t1/2) ranged from 1.5 to 3.6 hours.

The pharmacokinetics of laronidase were evaluated in 6-year-old or younger patients (N=7 to 9) with MPS I disease who received 0.58 mg/kg of body weight once weekly of ALDURAZYME as a 4-hour infusion in the open label clinical study (Study 3). After the 26th infusion, the 95% confidence interval of the geometric mean values of PK parameters ranged from 0.6 to 1.6 mcg/mL for the maximum plasma concentrations (Cmax), from 1.3 to 4.4 mcg ∙ hour/mL for area under the plasma concentration-time curve (AUC∞), from 0.12 to 0.56 L/kg for volume of distribution (Vz), from 2.2 to 7.7 mL/min/kg for plasma clearance (CL), and from 0.3 to 1.9 hours for elimination half-life (t1/2).

12.6 Immunogenicity

The observed incidence of anti-drug antibodies (ADA) is highly dependent on the sensitivity and specificity of the assay. Differences in assay methods preclude meaningful comparisons of the incidence of ADA in the studies described below with the incidence of ADA in other studies, including those of ALDURAZYME or of other laronidase products.

In clinical studies 1, 2, 3 [see Clinical Studies (14.1, 14.2)] and a dose-ranging clinical study that enrolled 8 patients between 3 to 17 years old who received once weekly intravenous doses of 0.58 mg/kg of ALDURAZYME, 70 of 73 (96%) of ALDURAZYME-treated patients developed IgG anti-laronidase antibodies (referred to as ADA). The 3 patients who did not develop ADA were patients with Hurler-Scheie forms of MPS I. In the 70 patients who developed ADA, the onset of ADA positivity in most patients occurred within 2 months after starting ALDURAZYME treatment. ADA titers peaked at approximately 4 months and generally declined over time. Higher ADA titers were observed in patients with Hurler forms of MPS I. Neutralizing antibodies that inhibited cellular uptake of laronidase were detected in 38 of 70 (54%) patients who developed ADA. Neutralizing antibodies that inhibited laronidase enzyme activity were detected in 1 of 70 (1.4%) patients who developed ADA.

Anti-Drug Antibody Effects on Pharmacokinetics

In Study 1, in some ALDURAZYME-treated patients who developed ADA the plasma clearance of laronidase at Week 12 was higher than that at Week 1, and patients with higher ADA titer had higher clearance. At Week 26, plasma clearance of laronidase was comparable to that at Week 1.

Anti-Drug Antibody Effects on Pharmacodynamics

Among the 70 ALDURAZYME-treated patients who developed ADA described above, patients with lower ADA titers tended to have greater than 50% reduction in urinary GAG (uGAG) levels at Week 26, while patients with higher ADA titers tended to have less than 50% reduction in uGAG levels. This correlation was observed in patients with Hurler-Scheie or Scheie form of MPS I. There was no clear correlation in patients with Hurler form of MPS I because these patients had high ADA titers and variable urinary GAG reductions. In postmarketing studies, an inverse correlation between percent uGAG reduction and ADA titer was observed in ALDURAZYME-treated patients who developed ADA. Patients with sustained ADA titers were more likely to have high ADA titers and tended to have less reduction in uGAG.

Anti-Drug Antibody Effects on Efficacy and Safety

In clinical studies, no correlation was demonstrated between the presence of ADA and therapeutic response for FVC or 6MWT.

In Study 1 and Study 2, 9 ALDURAZYME-treated patients who experienced severe infusion-associated reactions were tested for laronidase-specific IgE antibodies. One of the 9 patients tested positive for laronidase-specific IgE antibodies.

In the MPS I Registry, laronidase-specific IgE and IgG antibodies were evaluated in 10 ALDURAZYME-treated patients who had suspected hypersensitivity reactions and had an immunogenicity sample collected within seven days of event onset [see Adverse Reactions (6.1)]. Of the 10 patients, 9 tested positive for laronidase-specific IgE and/or IgG antibodies and 1 patient tested negative for both IgE and IgG antibodies.

In the postmarketing setting, five ALDURAZYME-treated patients who experienced anaphylaxis had ADA results available within seven days of event onset. Of these 5 patients, 3 patients tested positive for laronidase-specific IgE and/or IgG antibodies and in the other 2 patients, IgE antibodies were not detected and IgG antibody results were not reported.

13 NONCLINICAL TOXICOLOGY

13.1 Carcinogenesis, Mutagenesis, Impairment of Fertility

Animal studies to evaluate the mutagenic and carcinogenic potential of laronidase have not been conducted.

Laronidase at intravenous doses up to 3.6 mg/kg (6.2 times the recommended human dose) was found to have no effect on the fertility and reproductive performance of male and female rats.

14 CLINICAL STUDIES

14.1 Clinical Studies in Patients 6 Years and Older

Study 1 (NCT00912925) was a randomized, double-blind, placebo-controlled study in 45 patients with MPS I, including 1 patient with the Hurler form, 37 patients with Hurler-Scheie form, and 7 patients with Scheie form of MPS I. Among the 45 patients who completed Study 1, 22 (49%) were male and 23 (51%) were female ranging in age from 6 to 43 years with a mean age of 15.5 years. Thirty seven (82%) were White, 2 (4%) were Asian, 6 (13%) were Other and no patients were Black or African American. For ethnicity, 4 (9%) were Hispanic. All patients had a baseline percent predicted forced vital capacity (FVC) less than or equal to 77%. Patients received ALDURAZYME intravenously at 0.58 mg/kg of body weight once weekly or placebo once weekly for 26 weeks. All 45 randomized patients completed the study.

The primary efficacy outcome assessments were percent predicted FVC and distance walked in 6 minutes (6-minute walk test). After 26 weeks, patients treated with ALDURAZYME showed improvement in percent predicted FVC and in 6-minute walk test compared to placebo-treated patients (see Table 3).

Table 3: Change from Baseline in FVC [Forced Vital Capacity] and 6 Minute Walk Distance in ALDURAZYME or Placebo Treated Adult and Pediatric Patients with MPS I over 26 Weeks (Study 1)
 |  | ALDURAZYME® (N=22) | Placebo (N=23)
Forced Vital Capacity (percent of predicted normal)
Pretreatment Baseline | Mean ± s.d. | 48 ± 15 | 54 ± 16
Week 26 | Mean ± s.d. | 50 ± 17 | 51 ± 13
Change from Baseline to Week 26 | Mean ± s.d. | 1 ± 7 | -3 ± 7
Change from Baseline to Week 26 | Median | 1 | -1
Difference in Change from Baseline to Week 26 Between Groups | Mean | 4
Difference in Change from Baseline to Week 26 Between Groups | Median (95% CI) | 2 (0.4, 7), p=0.02 [By Wilcoxon Rank Sum Test]
6-Minute Walk Distance (meters)
Pretreatment Baseline | Mean ± s.d. | 319 ± 131 | 367 ± 114
Week 26 | Mean ± s.d. | 339 ± 127 | 348 ± 129
Change from Baseline to Week 26 | Mean ± s.d. | 20 ± 69 | -18 ± 67
Change from Baseline to Week 26 | Median | 28 | -11
Difference in Change from Baseline to Week 26 Between Groups | Mean | 38
Difference in Change from Baseline to Week 26 Between Groups | Median (95% CI) | 39 (-2, 79), p=0.07

Evaluations of bioactivity were changes in liver size and urinary GAG levels. Liver size and urinary GAG levels decreased in patients treated with ALDURAZYME compared to patients treated with placebo. No patient in the group receiving ALDURAZYME reached the normal range for urinary GAG levels during this 6-month study.

Study 2 (NCT00146770) was a 182-week, open-label, uncontrolled extension study of all 45 patients who completed Study 1. Patients received ALDURAZYME intravenously at 0.58 mg/kg body weight once weekly. Forty (89%) patients completed the study through Week 182. Five (11%) patients, all of whom received placebo in Study 1 and subsequently received Aldurazyme in Study 2 discontinued prematurely. Of these, 2 patients discontinued due to an adverse event, 2 patients due to patient wishes, and 1 patient due to pregnancy. For patients treated with ALDURAZYME, the mean increase in 6-minute walk test distance was maintained for an additional 182 weeks through completion of Study 2.

At the end of Study 2, the decrease in mean urinary GAG was similar to the decrease in urinary GAG reported in ALDURAZYME-treated patients at the end of Study 1. The relationship of urinary GAG to other measures of clinical response has not been established.

14.2 Clinical Studies in Patients 6 Years and Younger

Study 3 (NCT00146757) was a 52-week, open-label, uncontrolled clinical study in 20 patients with MPS I, including 16 patients (80%) with the Hurler form and 4 patients (20%) with the Hurler-Scheie form. Among the 20 patients who participated in Study 3, 12 (60%) were male and 8 (40%) were female ranging in age from 6 months to 5 years old with a mean age of 2.9 years. Eighteen (90%) were White, 1 (5%) were Black or African American and 1 (5%) were Other. A total of 18 patients completed the study. All 20 patients received ALDURAZYME intravenously at 0.58 mg/kg of body weight once weekly for 26 weeks. After 26 weeks of treatment, 16 patients continued to receive 0.58 mg/kg of body weight once weekly through Week 52, and 4 patients received 1.16 mg/kg of body weight once weekly from Week 26 through Week 52.

Reduction in mean urinary GAG was demonstrated at Week 13 and was maintained through Week 52. No patient receiving ALDURAZYME reached the normal range for urinary GAG levels during this 52-week study. Changes in urinary GAG levels in children 6 years and younger were similar to changes reported in older patients in Studies 1 and 2 (6 through 43 years old). The relationship of urinary GAG to other measures of clinical response has not been established.

16 HOW SUPPLIED/STORAGE AND HANDLING

ALDURAZYME (laronidase) injection is supplied as a colorless to pale yellow, clear to slightly opalescent solution in single-dose, clear Type I glass vial. Each vial contains 2.9 mg/5 mL (0.58 mg/mL) of laronidase. The closure consists of a siliconized butyl stopper and an aluminum seal with a plastic flip-off cap. ALDURAZYME is available as: One single-dose vial in a carton (NDC 58468-0070-1)

STORAGE AND HANDLING

Refrigerate vials of ALDURAZYME at 2°C to 8°C (36°F to 46°F). Do not freeze or shake. Protect from light. This product contains no preservatives.

17 PATIENT COUNSELING INFORMATION

Hypersensitivity Reactions (Including Anaphylaxis) and Infusion-Associated Reactions (IARs)

Advise the patient or caregiver that reactions related to the infusion may occur during and up to 3 hours after ALDURAZYME treatment, including life-threatening hypersensitivity reactions, including anaphylaxis, and IARs. Inform the patient and caregiver of the signs and symptoms of hypersensitivity reactions and IARs and to seek medical care should signs and symptoms occur [see Warnings and Precaution (5.1, 5.4)].

Cardiac and Respiratory Adverse Reactions

Advise the patient and/or caregiver to report immediately to a healthcare provider if signs or symptoms of cardiac or respiratory decompensation occur during or following an infusion [see Warnings and Precautions (5.2, 5.3)]. Inform patients using supplemental oxygen or continuous positive airway pressure (CPAP) during sleep to have these treatments readily available during infusion or extreme drowsiness/sleep induced by antihistamine use.

Registry

Inform the patient and/or caregiver that a registry for MPS I patients has been established in order to better understand the MPS I disease and to track clinical outcomes of patients with MPS I over time. Additionally, the MPS I Registry also monitors the effect of ALDURAZYME on pregnant women, lactating women, and their infants. Encourage the patient and/or caregiver to contact the registry program by visiting www.registrynxt.com or by calling 1-800-745-4447 ext. 15500.

ALDURAZYME is manufactured by:

BioMarin Pharmaceutical Inc.
  Novato, CA 94949
  US License Number 1649

ALDURAZYME is distributed by:

Genzyme Corporation
  Cambridge, MA 02141
  A SANOFI COMPANY

ALDURAZYME® is a registered trademark of BioMarin/Genzyme LLC. All rights reserved.

PRINCIPAL DISPLAY PANEL - 2.9 mg/5 mL Vial Label

NDC 58468-0070-1

ALDURAZYME®
(LARONIDASE)

2.9 mg/5 mL (0.58 mg/mL)

Injection
For Intravenous Infusion after Dilution

Rx Only

PRINCIPAL DISPLAY PANEL - 2.9 mg/5 mL Vial Carton

NDC 58468-0070-1

ALDURAZYME®
(LARONIDASE)

2.9 mg/5 mL (0.58 mg/mL)

Injection
For Intravenous Infusion after Dilution

One 5 mL single-dose vial

Rx Only

sanofi